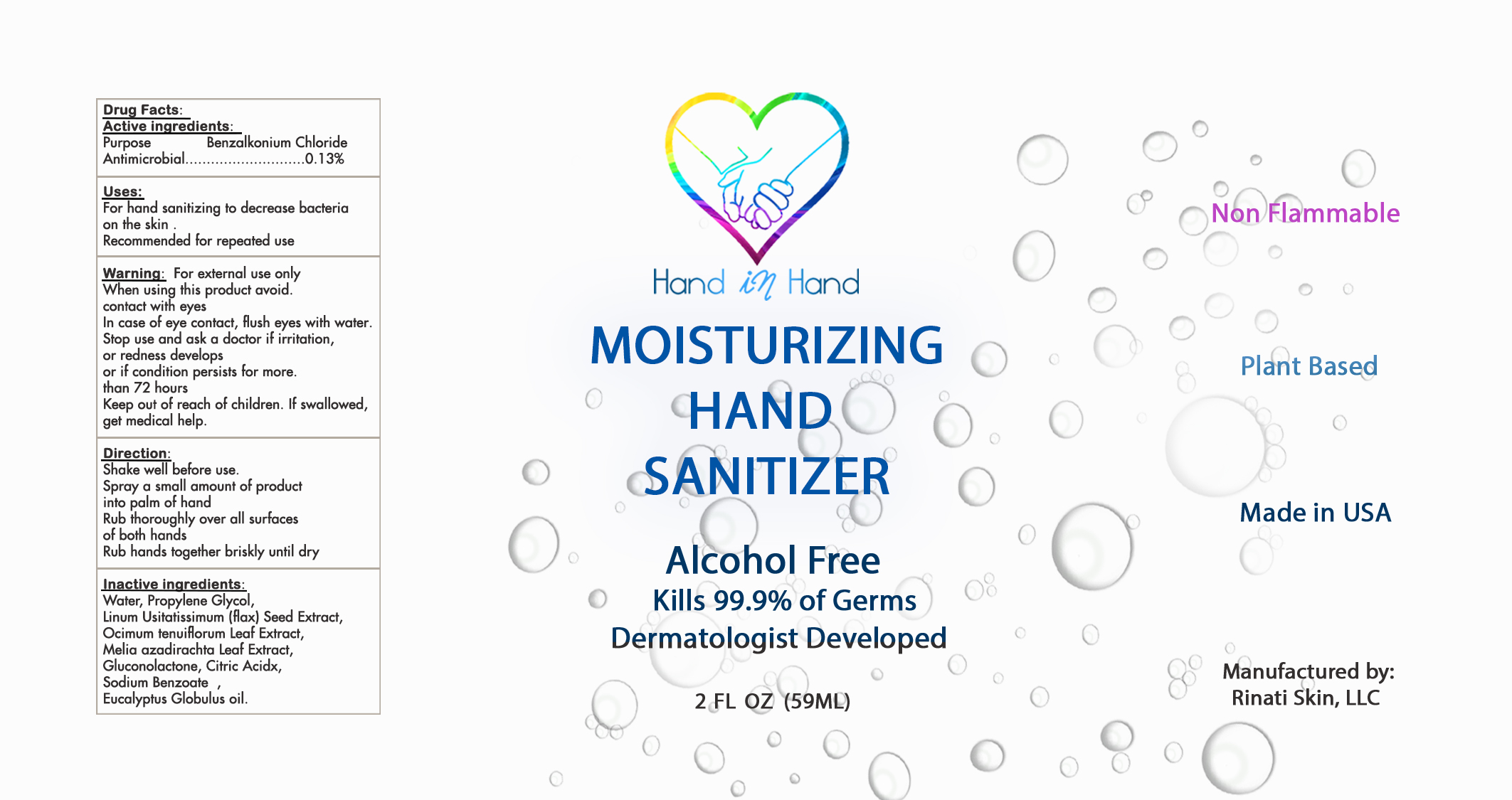 DRUG LABEL: MOISTURIZER HAND SANITIZER
NDC: 76849-101 | Form: SOLUTION
Manufacturer: Rinati Skin, LLC
Category: otc | Type: HUMAN OTC DRUG LABEL
Date: 20221028

ACTIVE INGREDIENTS: BENZALKONIUM CHLORIDE 0.13 g/100 mL
INACTIVE INGREDIENTS: WATER; PROPYLENE GLYCOL; FLAX SEED; OCIMUM TENUIFLORUM TOP; AZADIRACHTA INDICA LEAF; GLUCONOLACTONE; ANHYDROUS CITRIC ACID; SODIUM BENZOATE; EUCALYPTUS OIL

RINATI - MOISTURIZING HAND SANITIZER (76849-101)

ACTIVE INGREDIENT

BENZALKONIUM CHLORIDE 0.13%

PURPOSE

ANTIMICROBIAL

USE

FOR HAND SANITIZING TO DECREASE BACTERIA ON THE SKIN.

RECOMMENDED FOR REPEATED USE.

WARNINGS

FOR EXTERNAL USE ONLY.

WHEN USING THIS PRODUCT AVOID CONTACT WITH EYES.

IN CASE OF EYE CONTACT, FLUSH EYES WITH WATER. STOP USE AND ASK A DOCTOR IF IRRITATION, OR REDNESS DEVELOPS OR IF CONDITION PERSISTS FOR MORE THAN 72 HOURS.

KEEP OUT OF REACH OF CHILDREN.

IF SWALLOWED, GET MEDICAL HELP.

DIRECTIONS

SHAKE WELL BEFORE USE.

SPRAY A SMALL AMOUNT OF PRODUCT INTO PALM OF HAND.

RUB THOROUGHLY OVER ALL SURFACES OF BOTH HANDS.

RUB HANDS TOGETHER BRISKLY UNTIL DRY.

INACTIVE INGREDIENTS

WATER, PROPYLENE GLYCOL, LINUM USITATISSIMUM (FLAX) SEED EXTRACT, OCIMUM TENUIFLORUM LEAF EXTRACT, MELIA AZADIRACHTA LEAF EXTRACT, GLUCONOLACTONE, CITRIC ACID, SODIUM BENZOATE, EUCALYPTUS GLOBULUS OIL